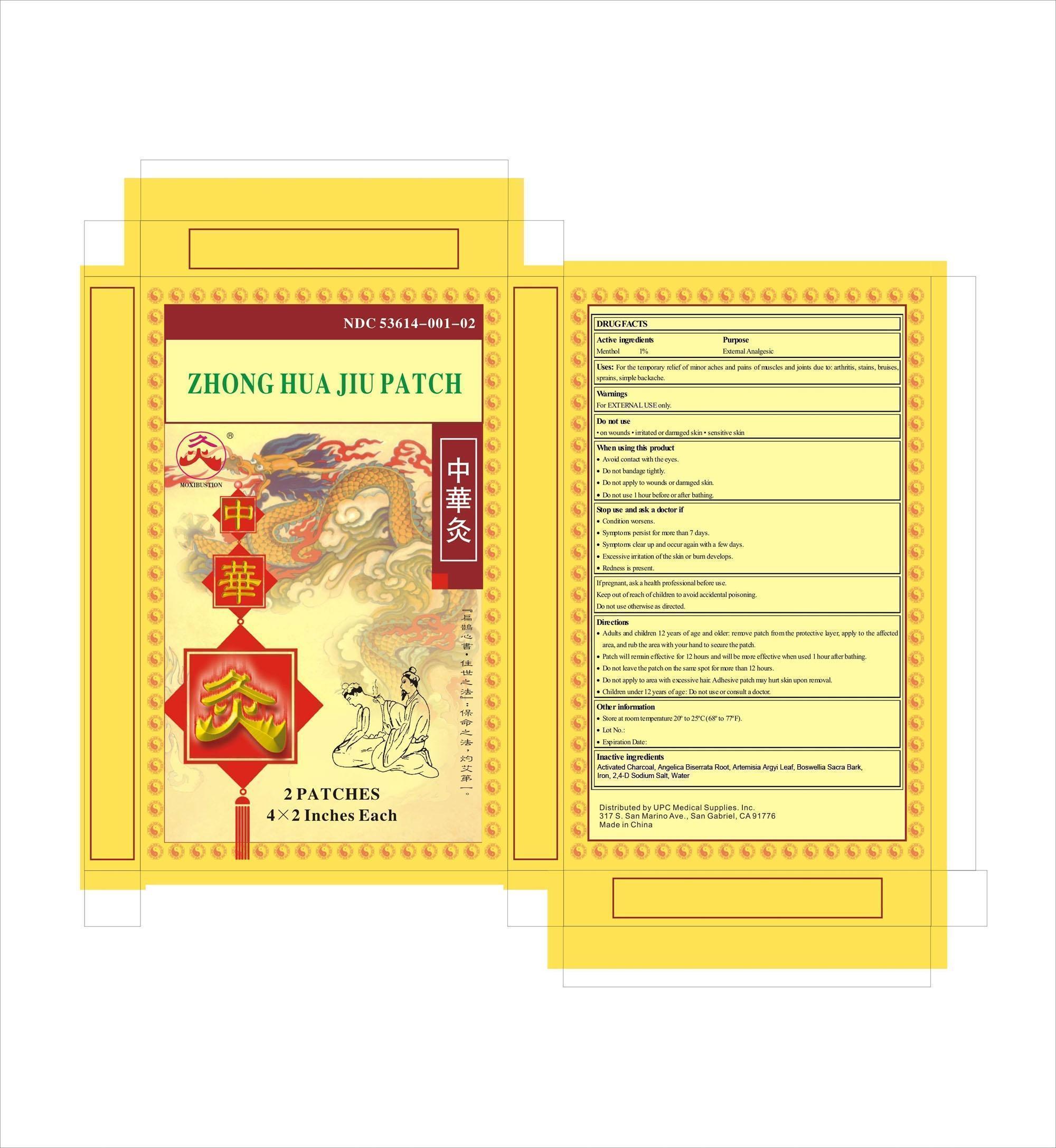 DRUG LABEL: ZHONG HUA JIU PATCH
NDC: 53614-001 | Form: PATCH
Manufacturer: Wuhan Chinese Moxibustion Technology Development Co.; Ltd.
Category: otc | Type: HUMAN OTC DRUG LABEL
Date: 20130305

ACTIVE INGREDIENTS: MENTHOL 10 mg/1000 mg
INACTIVE INGREDIENTS: ACTIVATED CHARCOAL 110.3 mg/1000 mg; ANGELICA BISERRATA ROOT 3 mg/1000 mg; ARTEMISIA ARGYI LEAF 15.4 mg/1000 mg; BOSWELLIA SACRA BARK 0.5 mg/1000 mg; IRON 683.1 mg/1000 mg; 2,4-D SODIUM SALT 11 mg/1000 mg; WATER 166.7 mg/1000 mg

ZHONG HUA JIU PATCH

ACTIVE INGREDIENTS

MENTHOL 1%

PURPOSE

EXTERNAL ANALGESIC

FOR THE TEMPORARY RELIEF OF MINOR ACHES AND PAINS OF MUSCLES AND JOINTS DUE TO: ARTHRITIS, STAINS, BRUISES, SPRAINS, SIMPLE BACKACHE.

WARNINGS

FOR EXTERNAL USE ONLY.

DO NOT USE

ON WOUNDS, IRRITATED OR DAMAGED SKIN, SENSITIVE SKIN

WHEN USING THIS PRODUCT

AVOID CONTACT WITH THE EYES

DO NOT BANDAGE TIGHTLY

DO NOT APPLY TO WOUNDS OR DAMAGED SKIN

DO NOT USE ONE HOUR BEFORE OR AFTER BATHING

STOP USE AND ASK A DOCTOR IF

CONDITION WORSENS

SYMPTONS PERSIST FOR MORE THAN SEVEN DAYS

SYMPTONS CLEAR UP AND OCCUR AGAIN WITH A FEW DAYS

EXCESSIVE IRRITATION OF THE SKIN OR BURN DEVELOPS

REDNESS IS PRESENT

PREGNANCY OR BREAST FEEDING

IF PREGNANT, ASK A HEALTH PROFESSIONAL BEFORE USE

DO NOT USE OTHERWISE AS DIRECTED

KEEP OUT OF REACH OF CHILDREN TO AVOID ACCIDENTAL POISONING

DIRECTIONS

ADULTS AND CHILDREN 12 YEARS OF AGE AND OLDER: REMOVE PATCH FROM THE PROTECTIVE LAYER, APPLY TO THE AFFECTED AREA, AND RUB THE AREA WITH YOUR HAND TO SECURE THE PATCH.

PATCH WILL REMAIN EFFECTIVE FOR 12 HOURS AND WILL BE MROE EFFECTIVE WHEN USED 1 HOUR AFTER BATHING.

DO NOT LEAVE THE PATCH ON THE SAME SPOT FOR MORE THAN 12 HOURS.

DO NOT APPLY TO THE AREA WITH EXCESSIVE HAIR. ADHESIVE PATCH MAY HURT SKIN UPON REMOVAL.

CHILDREN UNDER 12 YEARS OF AGE: DO NOT USE OR CONSULT A DOCTOR.

OTHER INFORMATION

STORE AT ROOM TEMPERATURE 20-25 DEGREES CENTIGRADE (68-77 DEGREES FAHRENHEIT)

INACTIVE INGREDIENTS

ACTIVATED CHARCOL

ANGELICA BISERRATA ROOT

ARTEMISIA ARGYI LEAF

BOSWELLIA SACRA BARK

IRON

2,4-D SODIUM SALT

WATER

Questions or comments?

Please call (626)285-1600 9:00 am - 5:30 pm PST